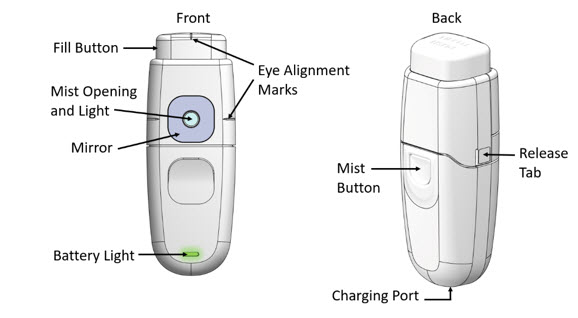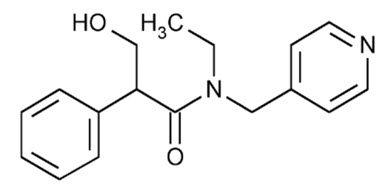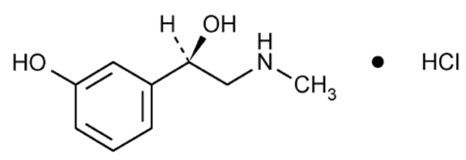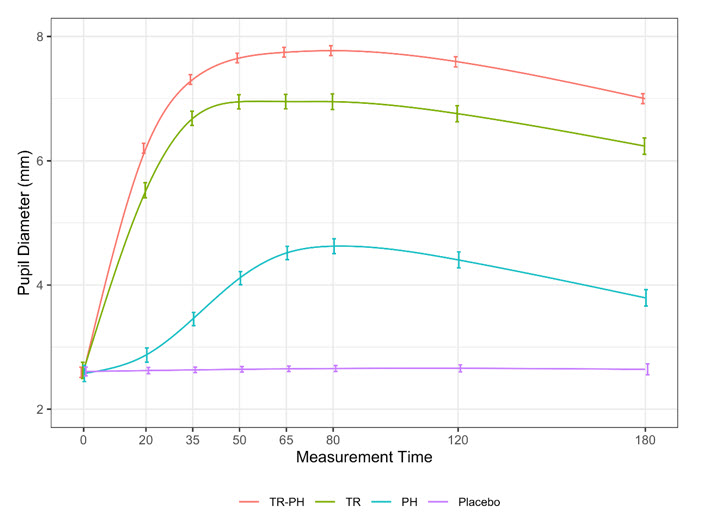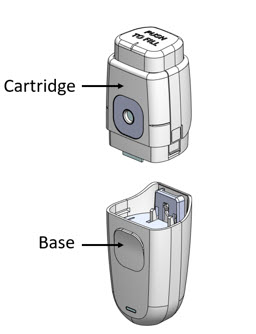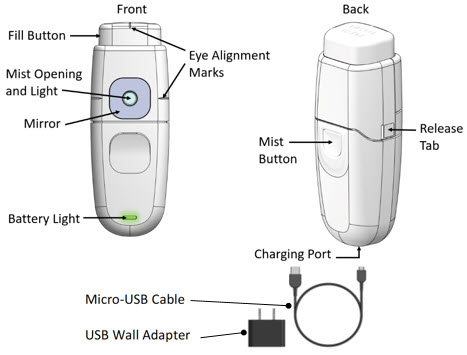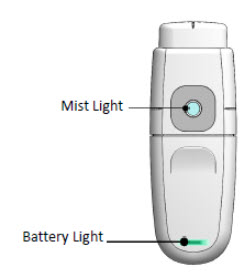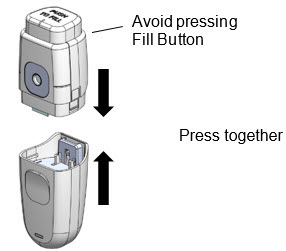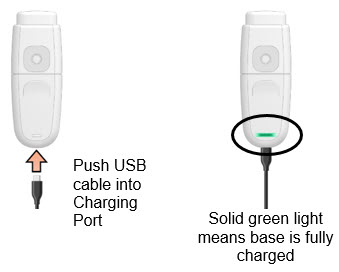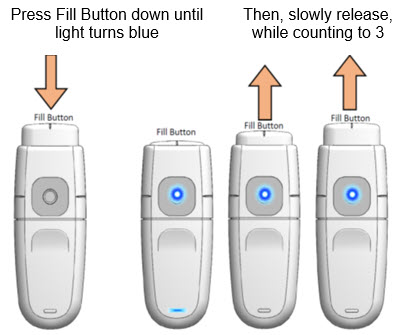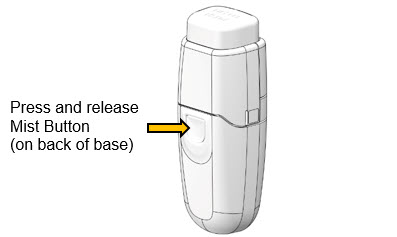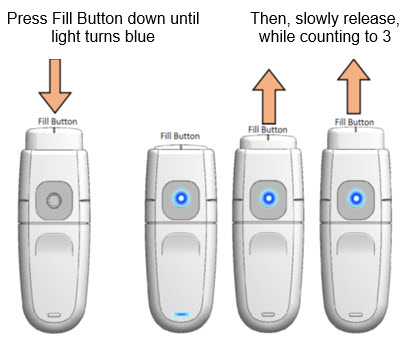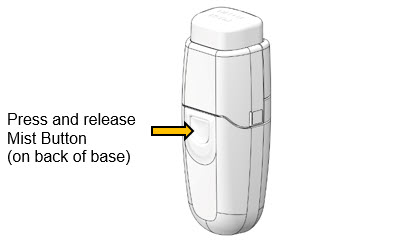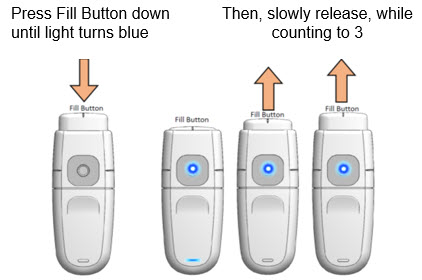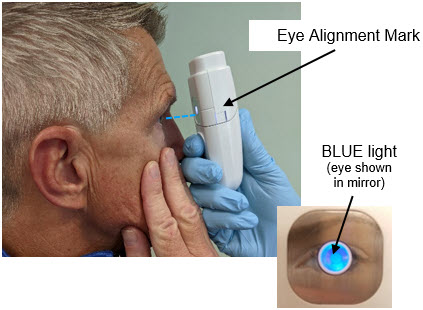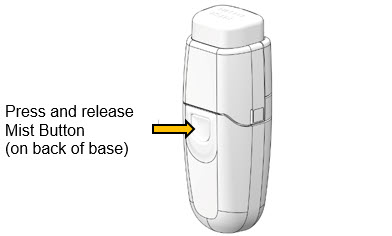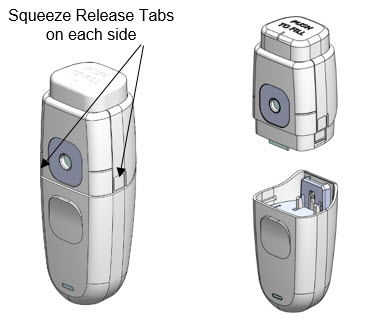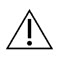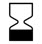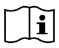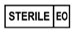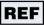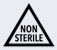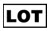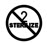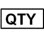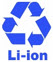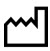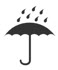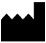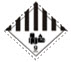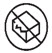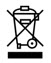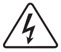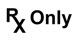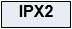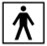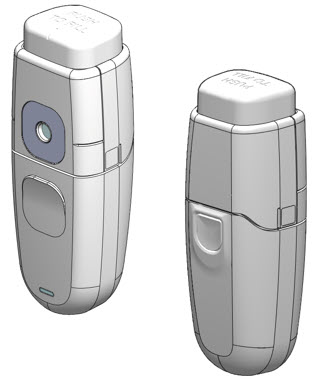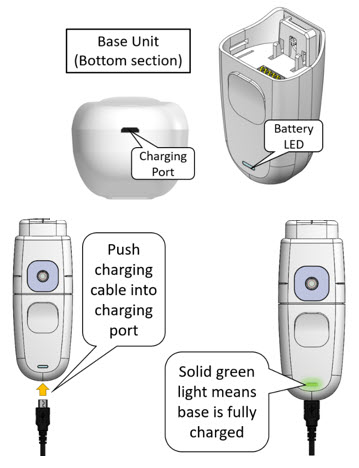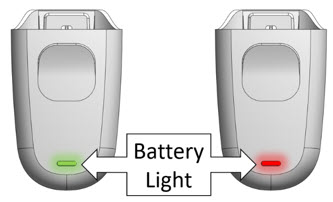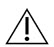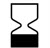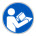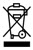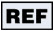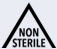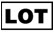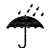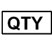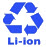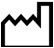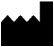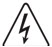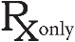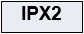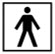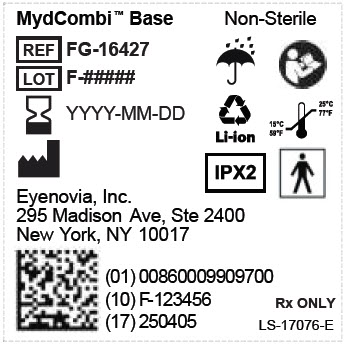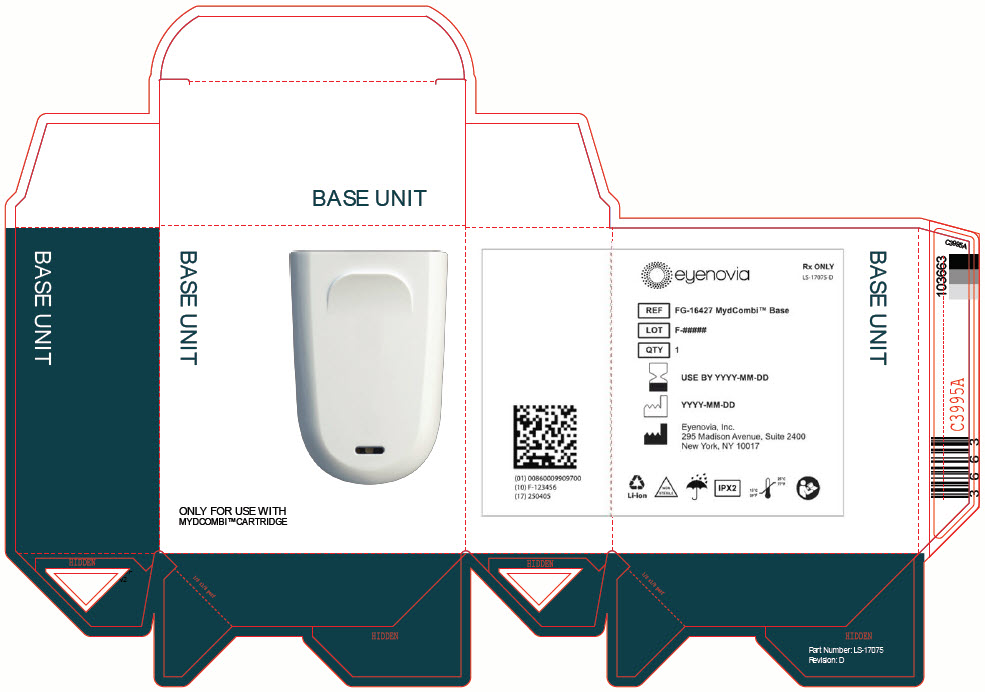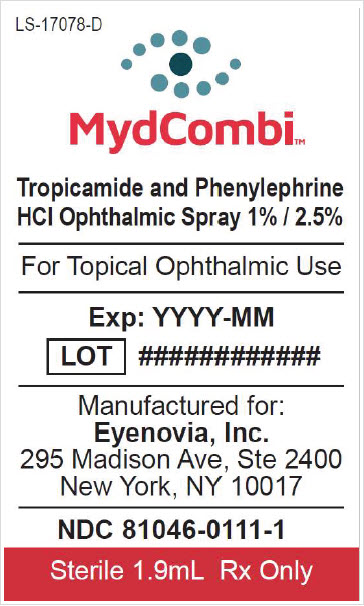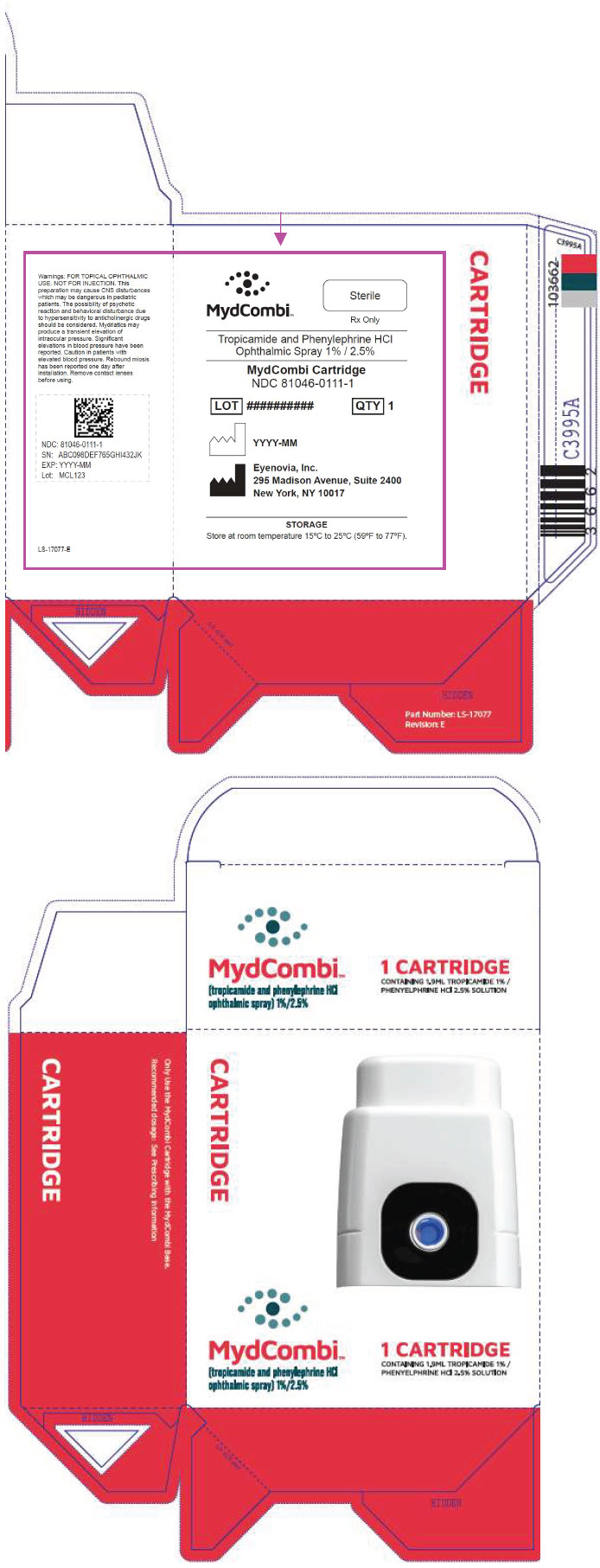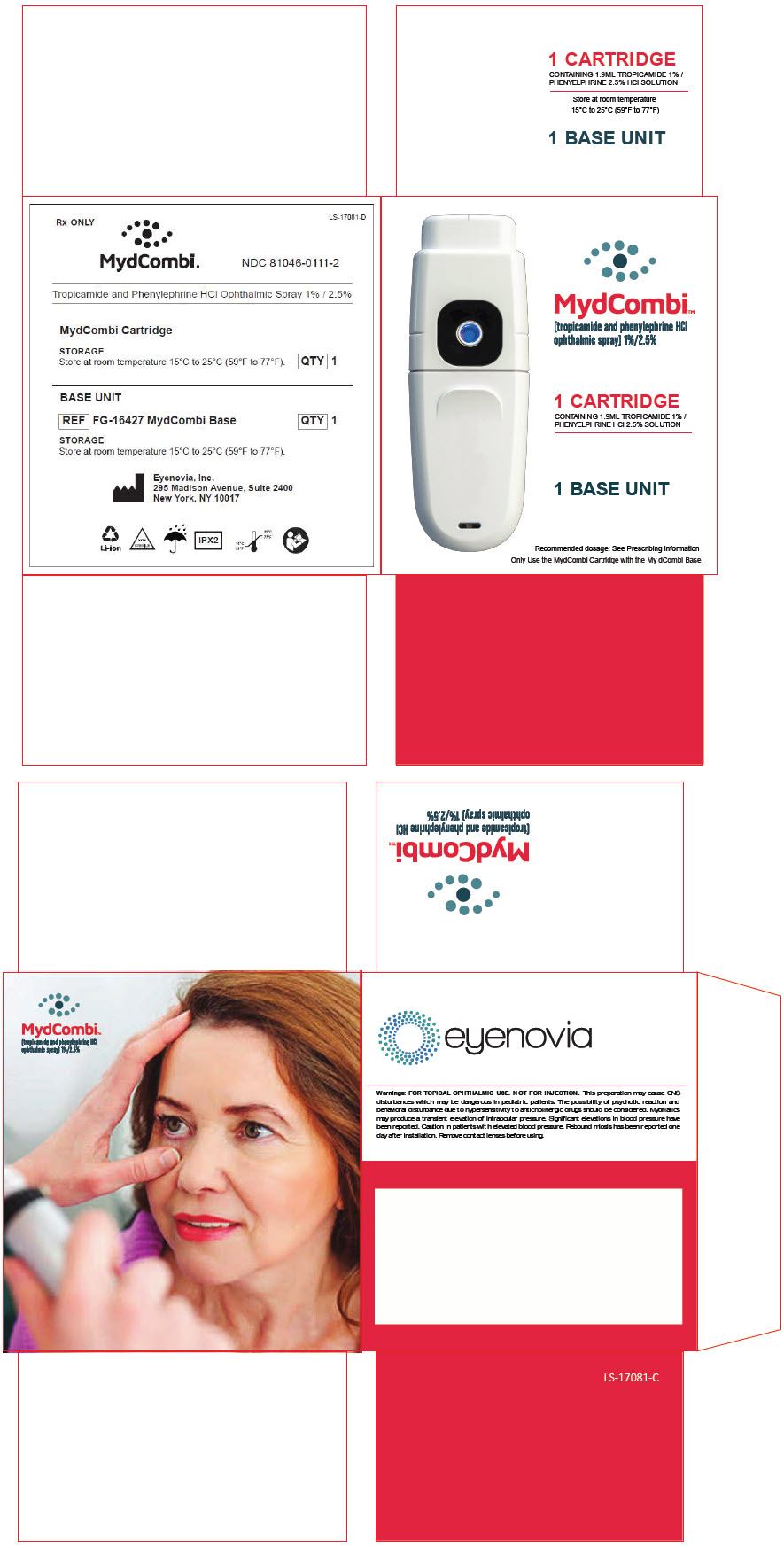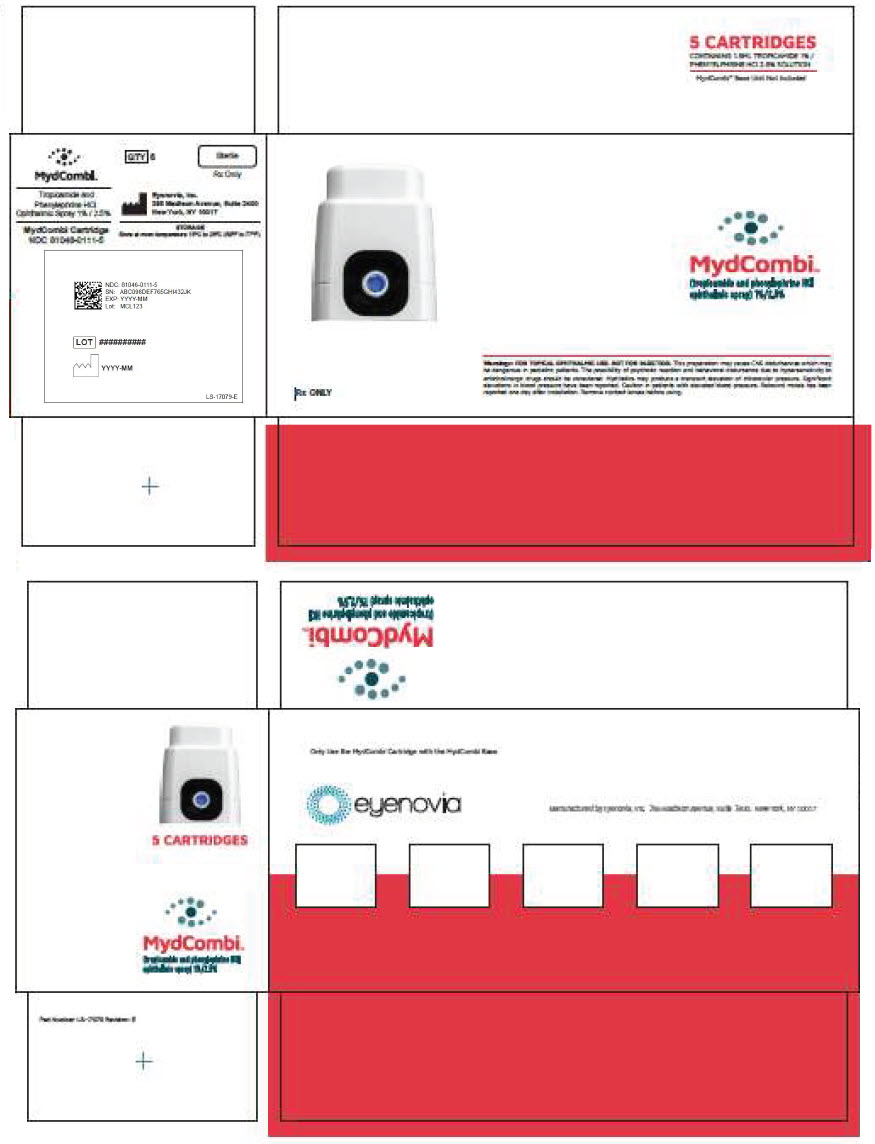 DRUG LABEL: MYDCOMBI
NDC: 81046-0111 | Form: SPRAY, METERED
Manufacturer: Eyenovia, Inc.
Category: prescription | Type: HUMAN PRESCRIPTION DRUG LABEL
Date: 20230509

ACTIVE INGREDIENTS: Tropicamide 0.08 mg/0.008 mL; Phenylephrine Hydrochloride 0.2 mg/0.008 mL
INACTIVE INGREDIENTS: Hydrochloric Acid; Sodium Hydroxide; Water; Benzalkonium Chloride

HIGHLIGHTS OF PRESCRIBING INFORMATION

These highlights do not include all the information needed to use MYDCOMBI® safely and effectively. See full prescribing information for MYDCOMBI.
MYDCOMBI (tropicamide and phenylephrine hydrochloride ophthalmic spray) 1%/2.5%, for topical ophthalmic use
Initial U.S. Approval: 2023

1 INDICATIONS AND USAGE

MYDCOMBI is a combination of tropicamide, an anticholinergic, and phenylephrine hydrochloride, an alpha-1 adrenergic receptor agonist indicated to induce mydriasis for diagnostic procedures and in conditions where short term pupil dilation is desired (1)

2 DOSAGE AND ADMINISTRATION

- Administer one metered spray to the cornea of each eye to be dilated. Repeat after 5 minutes. (2.1)
- In pediatric patients younger than 1 year old, administer one metered spray to the cornea of each eye to be dilated, up to a maximum of 3 sprays per eye per day (2.1)

3 DOSAGE FORMS AND STRENGTHS

Ophthalmic spray containing tropicamide 1% and phenylephrine hydrochloride 2.5%. Each metered spray delivers 0.008 mL which contains 0.08 mg tropicamide and 0.2 mg phenylephrine HCl (3)

4 CONTRAINDICATIONS

- Known hypersensitivity to any component of the formulation (4.1)

5 WARNINGS AND PRECAUTIONS

- Not for Injection: Topical ophthalmic use (5.1)
- Significant Elevations in Blood Pressure: Caution in pediatric patients less than 5 years of age, and in patients with cardiovascular disease or hyperthyroidism. In patients at high risk, monitor blood pressure post treatment (5.2)
- Central Nervous System Disturbances: Caution in pediatric patients where rare incidences of central nervous system disturbances have been reported (5.3)
- Intraocular Pressure: May produce a transient elevation (5.4)
- Rebound Miosis: Reported 1 day after administration (5.5)

6 ADVERSE REACTIONS

- Most common ocular adverse reactions include transient blurred vision, reduced visual acuity, photophobia, superficial punctate keratitis, and mild eye discomfort. Increased intraocular pressure has been reported following the use of mydriatics (6.1)
- Systemic adverse reactions including dryness of the mouth, tachycardia, headache, allergic reactions, nausea, vomiting, pallor, central nervous system disturbances and muscle rigidity have been reported with the use of tropicamide (6.2)

To report SUSPECTED ADVERSE REACTIONS, contact Eyenovia, Inc. at 1-833-393-6684 or FDA at 1-800-FDA-1088 or www.fda.gov/medwatch

7 DRUG INTERACTIONS

- Atropine-like Drugs: May exaggerate the adrenergic pressor response (7.1)
- Cholinergic Agonists and Ophthalmic Cholinesterase Inhibitors: May interfere with the antihypertensive action of carbachol, pilocarpine, or ophthalmic cholinesterase inhibitors (7.2)
- Potent Inhalation Anesthetic Agents: May potentiate cardiovascular depressant effects of (7.3)

8 USE IN SPECIFIC POPULATIONS

Pediatric Use: May rarely cause central nervous system disturbances which may be dangerous in pediatric patients (5.3, 8.4)

FULL PRESCRIBING INFORMATION

1 INDICATIONS AND USAGE

MYDCOMBI (tropicamide and phenylephrine hydrochloride ophthalmic spray) 1% / 2.5% is indicated to induce mydriasis for diagnostic procedures and in conditions where short term pupil dilation is desired.

2 DOSAGE AND ADMINISTRATION

2.1 Recommended Dosage

Administer one metered spray to the cornea of each eye to be dilated. Repeat after 5 minutes.

Pediatric Patients Younger Than 1 Year Old

In pediatric patients younger than 1 year old, administer one metered spray to the cornea of each eye to be dilated, up to a maximum of 3 sprays per eye per day.

2.2 Administration Instructions

The following steps should be followed sequentially:

1. Load the MYDCOMBI dispenser by depressing the FILL BUTTON at the top of the dispenser once.
  Figure 1: MYDCOMBI Dispenser Front (L) and Back (R) View
2. Hold MydCombi™ dispenser with thumb over Mist Button, wrapping other fingers around base.
3. Bring MydCombi™ dispenser to patient's eye with Mirror facing the eye.
  - The dispenser should be as close as patient's nose.
  - To prevent blinking, use your other hand to gently pull lower eyelid down or ask patient to pull her/his lid down.
4. Aim Mist Opening toward the center of eye.
5. Confirm Alignment Marks (on the Fill Button and the cartridge side) align with the center of eye.
  - Ask patient to confirm when their eye is centered on the BLUE Mirror.
  If patient is having trouble centering their eye on the blue light, ask that they look up, then look at the BLUE Mirror.
6. Firmly press and release Mist Button.
  - The drug solution should gently wet the eye. Repeat steps A to F if needed.
7. Administer a second metered spray after 5 minutes to each dilated eye.
8. Repeat steps A to G for the contralateral eye if it is to be dilated.

3 DOSAGE FORMS AND STRENGTHS

MYDCOMBI is a sterile, clear, colorless, topical ophthalmic spray containing tropicamide 1% (w/w) and phenylephrine hydrochloride 2.5% (w/w). Each metered spray delivers 0.008 mL which contains 0.08 mg tropicamide and 0.2 mg phenylephrine hydrochloride.

4 CONTRAINDICATIONS

4.1 Known Hypersensitivity

Contraindicated in persons showing known hypersensitivity to any component of the formulation.

5 WARNINGS AND PRECAUTIONS

5.1 Topical Ophthalmic Use

MYDCOMBI is not indicated for injection.

5.2 Blood Pressure Elevation

Caution should be exercised with the use of MYDCOMBI in pediatric patients less than 5 years of age and patients with hyperthyroidism, or cardiovascular disease. The post-treatment blood pressure of patients with cardiac and endocrine diseases and any patients who develop symptoms should be carefully monitored.

5.3 Central Nervous System Disturbances

Tropicamide in MYDCOMBI may cause CNS disturbances which may be dangerous in pediatric patients. The possibility of psychotic reactions and behavioral disturbances due to hypersensitivity to anticholinergic drugs should be considered.

5.4 Intraocular Pressure

Mydriatics may produce a transient elevation of intraocular pressure.

5.5 Rebound Miosis

Rebound miosis has been reported one day after receiving phenylephrine hydrochloride ophthalmic solution, and re-administration of the drug produced a lesser mydriatic effect.

6 ADVERSE REACTIONS

Because clinical trials are conducted under widely varying conditions, adverse reaction rates observed in the clinical trials of a drug cannot be directly compared to rates in the clinical trials of another drug and may not reflect the rates observed in practice. The most common adverse reactions (incidence < 2%) were transient blurred vision, reduced visual acuity, photophobia, and mild eye discomfort.

6.1 Ocular Adverse Reactions

Transient blurred vision, reduced visual acuity, photophobia, superficial punctate keratitis, and mild eye discomfort may occur. Increased intraocular pressure has been reported following the use of mydriatics.

6.2 Systemic Adverse Reactions

Dryness of the mouth, tachycardia, headache, allergic reactions, nausea, vomiting, pallor, central nervous system disturbances and muscle rigidity have been reported with the use of tropicamide. Psychotic reactions, behavioral disturbances, and vasomotor or cardiorespiratory collapse in children have been reported with the use of anticholinergic drugs.

A marked increase in blood pressure has been reported with the use of phenylephrine, particularly, but not limited to, low weight premature neonates, infants, and hypertensive patients.

7 DRUG INTERACTIONS

7.1 Agents That May Exaggerate Pressor Responses

Phenylephrine in MYDCOMBI may enhance the pressor effects of atropine-like drugs and induce tachycardia in some patients.

7.2 Cholinergic Agonists and Ophthalmic Cholinesterase Inhibitors

Tropicamide in MYDCOMBI may interfere with the antihypertensive action of carbachol, pilocarpine, or ophthalmic cholinesterase inhibitors.

7.3 Potent Inhalation Anesthetic Agents

Phenylephrine in MYDCOMBI may potentiate the cardiovascular depressant effects of some inhalation anesthetic agents.

8 USE IN SPECIFIC POPULATIONS

8.1 Pregnancy

Risk Summary

There are no available data on MYDCOMBI use in pregnant women or animals to inform any drug-associated risks. It is also not known whether tropicamide or phenylephrine can cause fetal harm when administered to a pregnant woman or can affect reproduction capacity. MYDCOMBI should be given to a pregnant woman only if clearly needed.

8.2 Lactation

Risk Summary

There are no data on the presence of tropicamide or phenylephrine in human milk from the administration of MYDCOMBI, the effects on the breastfed infant, or the effects on milk production. The developmental and health benefits of breastfeeding should be considered along with the mother's clinical need for MYDCOMBI and any potential adverse effects on the breastfed child from MYDCOMBI.

8.4 Pediatric Use

Tropicamide in MYDCOMBI may rarely cause CNS disturbances which may be dangerous in pediatric patients. Psychotic reactions, behavioral disturbances, and vasomotor or cardiorespiratory collapse in children have been reported with the use of anticholinergic drugs [see Warnings and Precautions (5.3)].

8.5 Geriatric Use

No overall differences in safety or effectiveness of MYDCOMBI have been observed between patients 65 years of age and older and younger adult patients.

10 OVERDOSAGE

Overdosage of MYDCOMBI may cause a rapid rise in blood pressure. It may also cause headache, anxiety, nausea and vomiting, and ventricular arrhythmias. Prompt injection of a rapidly acting alpha- adrenergic blocking agent such as phentolamine has been recommended.

11 DESCRIPTION

MYDCOMBI is a sterile, clear, colorless fixed dose combination of an anticholinergic (tropicamide) and an alpha-adrenergic receptor agonist (phenylephrine hydrochloride) for topical ophthalmic use. The 2 active ingredients are represented by the chemical structures below.

Tropicamide:

Chemical Name: Benzeneacetamide, N-ethyl-α-(hydroxymethyl)-N-(4-pyridinylmethyl)-

Molecular Formula: C17H20N2O2

Molecular Weight: 284.35 g/mol

Phenylephrine Hydrochloride:

Chemical Name: (R)-3-hydroxy-α[(methylamino)methyl]benzenemethanol hydrochloride

Molecular Formula: C9H13NO2∙HCl

Molecular Weight: 203.67 g/mol

Each mL of MYDCOMBI ophthalmic spray (sterile) contains: ACTIVES: Phenylephrine Hydrochloride 2.5% (25 mg) equivalent to 20.6 mg of phenylephrine base, Tropicamide 1% (10 mg); INACTIVE: Hydrochloric Acid and/or Sodium Hydroxide may be added to adjust pH (pH 4.8–5.2), Water for Injection; PRESERVATIVE: Benzalkonium Chloride 0.01% (0.1 mg).

12 CLINICAL PHARMACOLOGY

12.1 Mechanism of Action

Tropicamide, the anticholinergic component of MYDCOMBI, blocks the responses of the sphincter muscle of the iris, dilating the pupil (mydriasis). Phenylephrine hydrochloride, the alpha-1 adrenergic agonist component of MYDCOMBI, acts as a mydriatic agent by contracting the dilator muscle of the iris.

12.2 Pharmacodynamics

MYDCOMBI acts in 15 to 30 minutes with maximal mydriasis occurring in 20 to 90 minutes. Darker irides tend to dilate slower than lightly pigmented irides and to achieve maximal effect may require more doses than lighter irides.

Mydriasis will reverse spontaneously with time, with recovery after 3 to 8 hours. Complete recovery from mydriasis in some individuals may require 24 hours.

13 CLINICAL STUDIES

Two Phase 3 clinical trials were conducted to evaluate the efficacy of MYDCOMBI for achievement of mydriasis. The MIST-1 study was a prospective, double-masked, active-controlled, 3-period cross-over, superiority study to compare the pupil dilating effect of MYDCOMBI to tropicamide 1% and to phenylephrine 2.5%, with all solutions topically administered by the Optejet® Dispenser (N = 64 subjects; 128 eyes). The MIST-2 study was a prospective, multicenter, double-masked, placebo-controlled, 3-period crossover, superiority study to compare the pupil dilating effect of MYDCOMBI to placebo (eyewash solution), with both solutions topically administered by the Optejet Dispenser (N = 70 subjects; 140 eyes).

The primary efficacy endpoint for both studies was the mean change in 35-minute pupil diameter compared to baseline as measured by digital pupillometry in highly photopic conditions. Data from the 2 studies are presented in Table 1. At 35 minutes post-dose, the mean change in pupil diameter was 4.7 mm with MYDCOMBI, 4.1 mm with tropicamide, and 0.9 mm with phenylephrine in MIST-1, and was 4.8 mm with MYDCOMBI and 0.1 mm with placebo in MIST-2. MYDCOMBI was statistically superior to tropicamide administered alone and phenylephrine administered alone.

Table 1 Pupil Size and Change in Diameter from Baseline at 35 Minutes Post-Dose (MIST-1 and MIST-2) (Per-Protocol Population [The per-protocol (PP) population included all randomized subjects who received at least one dose of study medication and completed all planned assessments (related to the primary endpoint) without major protocol violations. Two subjects in MIST-1 and one subject in MIST-2 who withdrew consent after their first treatment visit were not included in the PP populations which resulted in 62 completed subjects (124 eyes) in MIST-1 and 69 completed subjects (138 eyes) in MIST-2 comprised the PP populations. Sensitivity analysis performed on the intent-to-treat (ITT) population including all randomized subjects resulted in consistent efficacy results.])
 | MIST-1 |  |  | MIST-2
Visit | MYDCOMBI (N = 124) | Tropicamide Alone (N = 124) | Phenylephrine Alone (N = 124) | MYDCOMBI (N = 138) | Placebo (N = 138)
Mean Baseline (SD) | 2.6 (0.05) | 2.6 (0.05) | 2.6 (0.05) | 2.6 (0.04) | 2.6 (0.04)
35-Minutes Post-Dose (SD) | 7.3 (0.08) | 6.7 (0.08) | 3.5 (0.08) | 7.3 (0.07) | 2.7 (0.05)
Change from Baseline (SD) | 4.7 (0.07) | 4.1 (0.06) | 0.9 (0.08) | 4.8 (0.07) | 0.1 (0.04)
Difference from MYDCOMBI (95% CI) [Treatment differences and 95% confidence interval estimates were based on a mixed model including treatment, eye, baseline diameter, and carryover effect (for MIST-2 study only). In both studies, an unstructured covariance structure was used to account for within-subject correlation between eyes.] | -- | 0.6 (0.4, 0.8) | 3.9 (3.7, 4.1) | -- | 4.7 (4.5, 4.8)
SD=Standard Deviation

MYDCOMBI provided a clinically significant effect in the proportion of eyes achieving pupil diameter of ≥ 6 mm at 35-minute post-dose in 94% of eyes compared to 78% of eyes administered tropicamide alone and 1.6% of eyes administered phenylephrine alone, and 0% of eyes administered placebo. As shown in Figure 2, peak effect was measured at the 80-minute evaluation when the mean change from baseline was 5.2 mm. Treatment differences in mydriasis were observed as early as 20 minutes and still present at 180 minutes post-dose, the end of the protocol-specified observation period.

Figure 2: MIST-1 and MIST-2 pooled, mean pupil diameter vs measurement time, by treatment group. Vertical bars show 95% confidence interval for the mean at each point. Smooth curves are based on an 8 degrees of freedom (df) generalized additive model (GAM) smooth through time, adjusting for baseline pupil diameter. Confidence intervals are not adjusted for correlation.

14 HOW SUPPLIED/STORAGE AND HANDLING

MYDCOMBI is supplied as sterile, clear, colorless solution in a 2 mL vial enclosed in a dispenser cartridge. Each MYDCOMBI cartridge holds approximately 180 sprays.

Do not tamper with or attempt to open the MYDCOMBI cartridge. Such action may damage the dispenser causing an incorrect medication discharge volume; additionally, the dispenser base may not function properly.

Only use the MYDCOMBI cartridge with the MYDCOMBI Dispenser base which may be supplied separately. The MYDCOMBI base will not work with any other cartridges.

NDC 81046-0111-1. Carton containing one replacement sterile drug cartridge

NDC 81046-0111-2. Box containing one carton with one sterile drug cartridge, and one carton with one base unit

NDC 81046-0111-5. Box containing five cartons, each with one replacement sterile drug cartridge

The MYDCOMBI cartridge must be used prior to the expiration date on the cartridge.

STORAGE AND HANDLING

Storage: Store at room temperature 15°C to 25°C (59°F to 77°F).

Manufactured for Eyenovia, Inc. by Alcami Corporation

15 PATIENT COUNSELING INFORMATION

Advise patients that they may experience sensitivity to light and blurred vision while their pupils are dilated.

Advise patients not to drive, use machinery, or do any activity that requires clear vision until they are sure they can perform such activities safely.

INSTRUCTIONS FOR USE

MydCombi™
(Tropicamide and Phenylephrine HCl Ophthalmic Spray), 1%/2.5%

Rx Only

Contents
Getting to know MydCombi™ | 3
How the MydCombi™ Dispenser Works | 3
Understanding the Mist and Battery Lights | 4
Important Reminders and Cleaning Instructions | 4
Storing the MydCombi™ Base and Cartridges | 5
Assembling the MydCombi™ Dispenser | 6
Preparing MydCombi™ for Use Each Day | 8
Administering MydCombi™ | 9
Troubleshooting Tips | 10
Replacing the MydCombi™ Cartridge | 10
Symbols Used in Labels on the MydCombi™ Cartridge, Base and Packaging | 11

INSTRUCTIONS FOR USE
MydCombi™ Ophthalmic Spray

This "Instructions for Use" document has information about the administration of MydCombi™ (Tropicamide and Phenylephrine HCI Ophthalmic Spray) 1%/2.5%.

MydCombi™ is packaged in a dispenser that mists drug solution onto the eye. It has 2 parts – the cartridge that holds the drug solution, and the base that holds electronics.

Getting to know MydCombi™

MydCombi™ Dispenser Parts

MydCombi™ Assembled

How the MydCombi™ Dispenser Works

- The MydCombi™ Cartridge holds the drug solution.
- The MydCombi™ Base supplies power to the dispenser.
- The Fill Button is pressed to load the drug solution for topical ophthalmic administration.
- The Mist Opening is where drug solution comes out when the Mist Button is pressed.
- The Light and Mirror around the Mist Opening and the Eye Alignment Marks on the top and each side of the cartridge help align the eye for drug administration.
- The Battery Light shows how much electrical charge remains in the Base.
- The Release Tabs on each side of the cartridge are used to separate the cartridge and base when replacing cartridges.
- The MydCombi™ Base is charged using a Micro-USB to USB Cable with Wall Plug or USB port (supplied separately). See "MydCombi™ Base Charging and Electrical Information" .

Understanding the Mist and Battery Lights

The Mist Light and the Battery Light show the status of the MydCombi™ dispenser.

 | What the Mist and Battery Lights Mean
 | If you see… | It means…
 | Mist Light SOLID BLUE | Ready to dose
 | Mist Light BLINKING BLUE with Battery Light BLINKING RED & BLUE | Reset the dispenser; - See "TROUBLESHOOTING TIPS" (page 10) for dispenser reset instructions.; If lights continue blinking after dispenser reset, reset again. If lights continue to blink after second reset, change the cartridge.
 | Battery Light BLINKING GREEN | Battery is charging
 | Battery Light SOLID GREEN | Battery is fully charged
 | Battery Light BLINKING RED | Battery is low
 | Battery Light SOLID RED | Charge dispenser base at once

Important Reminders and Cleaning Instructions

- Wash hands prior to using MydCombi™.
- Before each use, the exterior (including the mirror surface) of the dispenser should be cleaned using a 70% isopropyl alcohol (IPA) wipe or a clean dust-free, cotton cloth dampened with 70% IPA solution.
- Wipe the exterior for 3 minutes. While wiping, pay close attention to all cracks, crevices, and any other hard to reach areas. Additional wipes may be used as needed. Allow the exterior to air dry. Only manual, non-immersion cleaning as described should be used for the dispenser. Do not autoclave (steam sterilize) or immerse in cleaning fluids. Always disconnect power supply from source before cleaning.
- If the patient wears soft contact lenses, they should be removed at least 10 minutes before drug administration.
- If the patient uses artificial tears, they should not be administered within 10 minutes of drug administration.
- Each MydCombi™ cartridge holds approximately 180 sprays.
- Only use the MydCombi™ cartridge with the MydCombi™ base. The MydCombi™ base will not work with any other type of cartridges.
- See "MydCombi™ Base Charging and Electrical Information" contained with MydCombi™ for complete instruction on charging and applicable electrical information.

Storing the MydCombi™ Base and Cartridges

Store MydCombi™ bases and cartridges at room temperature 15°C to 25°C (59°F to 77°F). Protect from light and excessive heat.

- Do not heat or freeze the MydCombi™ base or cartridge.
- Do not expose MydCombi™ base to fluids.
- Do not tamper with or try to open the MydCombi™ cartridge or base. Doing so could cause damage and result in personal injury.

The MydCombi™ base contains a lithium-ion battery. Damage to the base can cause fire. Do not puncture base or expose to excessive heat (≥ 50°C).

Li-Ion batteries may pose environmental and safety hazards and should be disposed of in accordance with all applicable Federal and State Laws. Check with all governing travel bodies for current requirements before air travel.

Assembling the MydCombi™ Dispenser

Complete these steps to assemble the MydCombi™ base and cartridge.

Note: If packaging is opened or damaged, do not use the contents. Instead, open a new base or cartridge, and contact your distributer for a replacement.

1. Assemble
  a. Remove base and/or cartridge from packaging.
  b. Align base and cartridge, then press together until they click.
    - Take care to avoid pressing Fill Button when assembling.

2. Charge
  Charge MydCombi™ base before first use (see "MydCombi Base Charging and Electrical Information" contained with MydCombi™ base packaging). Charging may be performed either before or after assembly.
  a. Push micro-USB cable into Charging Port.
  b. Connect opposite end of USB cable to wall outlet plug or USB port.
    - Battery light BLINKS GREEN while charging.
  c. Charge until battery light turns SOLID GREEN, then disconnect cable from Charging Port.
  Note: Excessive charging may damage battery or decrease battery life. Charging weekly, or when the Battery Light begins blinking red (signaling low battery) is recommended.

3. Prime
  a. Hold MydCombi™ dispenser upright.
  b. Firmly press Fill Button down until it stops, and Mist Light turns Blue.
  c. Slowly release Fill Button, while counting to 3.
    - If Fill Button does not return to position, press again until it is all the way down.
    - If Fill Button still does not return to position, get a new cartridge, and re-assemble (Steps 1 - 2 [page 6]).

  d. Point Mist Opening away from face.
  e. Firmly press, then release Mist Button.
  f. Repeat Steps a – e until mist emerges from opening.
    - If mist does not come out after repeating these steps 5 times, get a new cartridge and re-assemble (Steps 1 - 2 [page 6]).
4. MydCombi™ is now ready to use.

Preparing MydCombi™ for Use Each Day

Important: A test mist must be performed each day before dosing is commenced.

1. Load drug solution
  a. Hold MydCombi™ dispenser upright.
  b. Firmly press Fill Button down until it stops, and Mist Light turns Blue.
  c. Slowly release Fill Button, while counting to 3.
    - If Fill Button does not return to position, press again until it is all the way down.
    - If Fill Button still does not return to position, get a new cartridge, and re-assemble (Steps 1 - 2 [page 6]).

2. Do a test mist
  a. Holding MydCombi™ dispenser upright, point Mist Opening away from face.
  b. Firmly press and release Mist Button.
3. MydCombi™ is ready to use.

Administering MydCombi™

Important: Keep MydCombi™ dispenser upright during use to maintain dose volume.

1. Load drug solution
  a. Hold MydCombi™ dispenser upright and firmly press Fill Button down until it stops, and Mist Light turns Blue.
  b. Slowly release Fill Button, while counting to 3.

2. Align MydCombi™ with patient's eye
  a. Hold MydCombi™ dispenser with thumb over Mist Button, wrapping other fingers around base.
  b. Bring MydCombi™ dispenser to patient's eye with Mirror facing the eye.
    - The dispenser should be as close as patient's nose.
    - To prevent blinking, use your other hand to gently pull lower eyelid down or ask patient to pull her/his lid down.
  c. Aim Mist Opening toward the center of eye.
  d. Confirm Alignment Marks (on the Fill Button and the cartridge side) align with the center of eye.
    - Ask patient to confirm when their eye is centered on the BLUE Mirror.
  If patient is having trouble centering their eye on the blue light, ask that they look up, then look at the BLUE Mirror.

3. Press Mist Button
  a. Firmly press and release Mist Button.
    - The drug solution should gently wet the eye. Repeat Steps 1-3 if needed.

Troubleshooting Tips

1. If no mist comes out when Mist Button is pressed, confirm Fill Button has been pressed down completely, and has returned to the "up" position.
2. If solution is not administered within 1 minute after loading, it will be automatically discharged - the MIST Light will blink blue while the Battery Light blinks red and blue. The MydCombi™ dispenser must be reset using the steps below.
  To reset dispenser:
  - Press and release Mist Button.
  - Press and release Fill Button.
  - Press and release Mist Button again.
  - Reload solution (Step 1 [page 9]).

To report suspected adverse reactions please contact Eyenovia, Inc at 1-833-393-6684 (Option 1) or FDA at 1-800-FDA-1088 or http://www.fda.gov/medwatch.

Replacing the MydCombi™ Cartridge

1. Remove cartridge
  a. Hold MydCombi™ base in one hand. With other hand, press and squeeze Release Tabs on each side of cartridge.
  b. Pull cartridge and base apart.
  c. Place used cartridge in original tray and box for disposal or recycling.

Symbols Used in Labels on the MydCombi™ Cartridge, Base and Packaging

SYMBOL | DEFINITION |  | SYMBOL | DEFINITION
 | CAUTION, CONSULT ACCOMPANYING DOCUMENTS |  |  | USE BY (YYYY-MM: YEAR-MONTH)
 | SEE INSTRUCTIONS FOR USE |  |  | STERILIZED USING ETHYLENE OXIDE
 | CATALOG NUMBER |  |  | NON-STERILE
 | BATCH CODE |  |  | DO NOT RESTERILIZE
 | QUANTITY |  |  | LITHIUM-ION BATTERY - TO BE APPROPRIATELY RECYCLED
 | DATE OF MANUFACTURE (YYYY-MM : YEAR-MONTH) |  |  | KEEP DRY
 | MANUFACTURER |  |  | GHS LITHIUM-ION DISPOSAL
 | DO NOT USE IF THE PACKAGING HAS BEEN OPENED OR DAMAGED |  |  | ELECTRONIC EQUIPMENT. DO NOT THROW IN TRASH.
 | WARNING: ELECTRICITY |  |  | BY PRESCRIPTION ONLY
 | PROTECTED AGAINST VERTICALLY FALLING WATER DROPS UP TO 15-DEGREE ANGLE |  |  | TYPE BF PART COMPLYING WITH IEC 60601-1

Manufactured By:
Eyenovia
295 Madison Ave., Suite 2400
New York, NY 10017

© 2022 Eyenovia, Inc. All rights reserved.

Mydcombi™ Base Charging and Electrical Information

Table of Contents
1. Charging the Mydcombi™ Base | 3
2. Specifications for Mydcombi Base and Charger | 4
3. EMC | 5
4. Disposal | 7
5. Notes on Safety | 7
6. Reporting to Manufacturer and Authorities | 7
7. Symbols Used in Labels on Mydcombi™ Base and Packaging | 8

1. Charging the Mydcombi™ Base

NOTE: Do not use base if packaging is opened or damaged. Get a new package by contacting your Eyenovia sales representative or calling 1-833-393-6684 (choose Option 1).

Type of Charger: Micro-USB to USB Cable with Wall Plug or USB port (see section 2 for specifications)
Charge Mydcombi™ Base Before First Use
 | Charging may be performed either before or after assembly with Mydcombi™ cartridge. Refer to "Instructions for Use - Mydcombi™ Ophthalmic Spray" for information on cartridge/base assembly and drug administration. Perform the following steps to charge base:; 1. Push micro-USB cable into charging port. 2. Connect opposite end of USB cable to wall outlet plug or USB port. - Battery light BLINKS GREEN while charging. 3. Charge until battery light turns SOLID GREEN, then disconnect cable from base.; Note: Excessive charging may damage battery or decrease battery life. Charging weekly, or when the LED light begins blinking red (signaling low battery), is recommended.
Battery Indicators on Mydcombi™ Base
 | If Battery Light is… | It means…
 | BLINKING GREEN | Battery is charging
 | SOLID GREEN | Battery is fully charged
 | BLINKING RED | Battery is low
 | SOLID RED | Charge base at once

2. Specifications for Mydcombi Base and Charger

Base Specifications
Parameter | Specifications
Operating power | 4.1VDC
Power source | Internally powered, Lithium-Ion Battery
Instrument make / model | Eyenovia / Mydcombi™ Base
Dimensions | 50 length, 120mm height, 40mm width (When assembled with cartridge)
Weight (system) | < 100g (When assembled with cartridge)
Allowed operating temperature range | 15°C to 25°C (59°F to 77°F)
Allowed shipping and storage temperature range | 15°C to 25°C (59°F to 77°F) at relative humidity of 15% to 90% RH, non-condensing
Allowed operation, storage, and shipping humidity range | 15°C to 25°C (59°F to 77°F) at relative humidity of 15% to 90% RH, non-condensing
Allowed operation, storage, and shipping atmospheric pressure | 700hPa to 1060hPa
Electrical shock protection - Classification / Degree | Internally powered Class I
Battery life | 2-4 weeks, if used as indicated.
Use Life | Do not use base longer than 12 months from date of first use, or after Use By Date
Software version | Software version number can be obtained by calling the manufacturer.

Charger Specifications (Micro-USB to USB Cable with Wall Plug or USB port)
Parameter | Specifications
Type | Switching Power Supply
Input | 100-240V~, 50/60 Hz 200mA
Output | 5V, 1A
USB Cable Minimum Requirements | 5V, 1A
USB cable must be UL Listed. Must meet US Standard Level VI energy efficiency. Must meet DOE & CEC regulatory requirements.
Examples of acceptable cables include those with UL number E178074 or Homespot Model S005AYU0500100.

3. EMC

This device has been tested and found to comply with the limits for a Class B digital device, pursuant to part 15 of the FCC Rules. These limits are designed to provide reasonable protection against harmful interference in professional medical equipment. This equipment generates, uses, and radiates radio frequency energy and, if not prepared and used in accordance with instructions, may cause harmful interference to radio communications. There is no guarantee, however, that interference will not occur in a particular setting. If this device does cause harmful interference to radio or television reception, which can be determined by turning the device off/on, the user is encouraged to try to correct the interference by one or more of the following measures:

- Reorient or relocate the receiving antenna
- Increase the separation between the device and receiver
- Connect the device into an outlet on a circuit different from that to which the receiver is connected
- Consult the dealer or an experienced radio/TV technician for help

Note: Changes or modifications not expressly approved by the party responsible for compliance could void the user's authority to operate the device.

Guidance and Manufacturer's Declaration

This device is intended for use in the electromagnetic environment specified below. The device user should assure use in such an environment.

Electromagnetic emissions
Emissions Test |  | Compliance
RF emissions CISPR 11 |  | Group 1
RF emissions CISPR 11 |  | Class B
Harmonic Emissions IEC 61000-3-2 |  | Class B
Voltage Fluctuations/Flicker emissions IEC 61000-3-3 |  | Complies
Electromagnetic immunity
Phenomena of a continuous nature |  | Shall operate as intended. Shall be no degradation of performance. Shall be no loss of function.
Phenomena of transient nature |  | Functions shall be self-recoverable. Shall operate as intended after recovering. Shall be no degradation of performance,
Power interruption exceeding a certain time |  | Functions shall be recoverable by the operator. Shall operate as intended after recovering. Shall be no degradation of performance.
Immunity Test | IEC 60601 Test Level |  | Compliance Level
Electrostatic fast transient/burst IEC 61000-4-4 (Charging Only) | ±2 kV for power supply lines |  | ±2 kV for power supply lines
Surge IEC 61000-4-5 EN/IEC 61000-4-3 L-N (Charging Only) | ±1 kV differential mode |  | ±1 kV differential mode
EN/IEC 61000-4-3 (Charging Only) | Radiated Immunity 3 V/m, 80 – 2700 MHz 80% AM at 1 kHz & Proximity Fields from RF Wireless Communications Equipment |  | Radiated Immunity 3 V/m, 80 – 2700 MHz 80% AM at 1 kHz & Proximity Fields from RF Wireless Communications Equipment
Voltage dips, short interruptions, and voltage variations on power supply input lines IEC 61000-4-11 | Voltage Dips 30% reduction, 25/30 periods At 0° |  | Voltage Dips 30% reduction, 25/30 periods At 0°
Voltage dips, short interruptions, and voltage variations on power supply input lines IEC 61000-4-11 | Voltage Dips > 95% reduction, 0.5 period At 0°, 45°, 90°, 135°, 180°, 225°, 270°, and 315° |  | Voltage Dips > 95% reduction, 0.5 period At 0°, 45°, 90°, 135°, 180°, 225°, 270°, and 315°
Voltage dips, short interruptions, and voltage variations on power supply input lines IEC 61000-4-11 | Voltage Dips > 95 reduction, 1 period At 0° |  | Voltage Dips > 95 reduction, 1 period At 0°
Voltage dips, short interruptions, and voltage variations on power supply input lines IEC 61000-4-11 | Voltage Interruptions > 95% reduction, 250/300 periods |  | Voltage Interruptions > 95% reduction, 250/300 periods
Conducted RF EN/IEC 61000-4-6 | Continuous Conducted RF, 80% AM (1 kHz) 3 Vrms, 0.15-80 MHz 6 Vrms in ISM and amateur radio Bands within 150kHz – 80MHz |  | Continuous Conducted RF, 80% AM (1 kHz) 3 Vrms, 0.15-80 MHz 6 Vrms in ISM and amateur radio Bands within 150kHz – 80MHz
Magnetic field IEC 61000-4-8 | Power Frequency Magnetic Field 30Arms/m at 50/60Hz |  | Power Frequency Magnetic Field 30Arms/m at 50/60Hz

Immunity to RF Wireless Communications Equipment
Test Frequency (MHz) | Band [For some services, only uplink frequencies are included.] (MHz) | Service | Modulation [The carrier shall be modulated using a 50% duty cycle square wave signal.] | Max. Power (W) | Distance (m) | Immunity test level (V/m)
385 | 380 –390 | TETRA 400 | Pulse 18 Hz | 1.8 | 0.3 | 27
450 | 430 – 470 | GMRS 460, FRS 460 | FM [As an alternative to FM modulation, 50% pulse modulation at 18 Hz may be used because, while it does not represent actual modulation, it would be worst case.] ± 5 kHz Deviation 1 kHz sine | 2 | 0.3 | 28
710 | 704 – 787 | LTE Band 13, 17 | Pulse 217 Hz | 0.2 | 0.3 | 9
745 | 704 – 787 | LTE Band 13, 17 | Pulse 217 Hz | 0.2 | 0.3 | 9
780 | 704 – 787 | LTE Band 13, 17 | Pulse 217 Hz | 0.2 | 0.3 | 9
810 | 800 – 960 | GSM 800/900, TETRA 800, iDEN 820, CDMA 850, LTE Band 5 | Pulse 18 Hz | 2 | 0.3 | 28
870 | 800 – 960 | GSM 800/900, TETRA 800, iDEN 820, CDMA 850, LTE Band 5 | Pulse 18 Hz | 2 | 0.3 | 28
930 | 800 – 960 | GSM 800/900, TETRA 800, iDEN 820, CDMA 850, LTE Band 5 | Pulse 18 Hz | 2 | 0.3 | 28
1720 | 1 700 – 1 990 | GSM 1800; CDMA 1900; GSM 1900; DECT; LTE Band 1, 3, 4, 25; UMTS | Pulse 217 Hz | 2 | 0.3 | 28
1845 | 1 700 – 1 990 | GSM 1800; CDMA 1900; GSM 1900; DECT; LTE Band 1, 3, 4, 25; UMTS | Pulse 217 Hz | 2 | 0.3 | 28
1970 | 1 700 – 1 990 | GSM 1800; CDMA 1900; GSM 1900; DECT; LTE Band 1, 3, 4, 25; UMTS | Pulse 217 Hz | 2 | 0.3 | 28
2450 | 2 400 – 2 570 | Bluetooth, WLAN, 802.11 b/g/n, RFID 2450, LTE Band 7 | Pulse 217 Hz | 2 | 0.3 | 28
5240 | 5 100 – 5 800 | WLAN 802.11 a/n | Pulse 217 Hz | 0.2 | 0.3 | 9
5500 | 5 100 – 5 800 | WLAN 802.11 a/n | Pulse 217 Hz | 0.2 | 0.3 | 9
5785 | 5 100 – 5 800 | WLAN 802.11 a/n | Pulse 217 Hz | 0.2 | 0.3 | 9

Recommended separation distances between portable and mobile RF communications equipment and the device, except for the distances indicated in the following table "Immunity to RF Wireless Communications Equipment".
The device is intended for use in an electromagnetic environment in which radiated RF disturbances are controlled. Users can help prevent electromagnetic interference by maintaining a minimum distance between portable and mobile RF communications equipment (transmitters) and the device as recommended below, according to the maximum output power of the communications equipment.
Rated maximum output power of transmitter (W) | Separation distance according to frequency of transmitter (m)
Rated maximum output power of transmitter (W) | 150 kHz to 80 MHz d = 1.2√P | 80 MHz to 800 MHz d = 1.2√P | 800 MHz to 2.7 GHz d = 2.3√P
0.01 | 0.12 | 0.12 | 0.23
0.1 | 0.38 | 0.38 | 0.73
1 | 1.2 | 1.2 | 2.3
10 | 3.8 | 3.8 | 7.3
100 | 12 | 12 | 23
For transmitters rated at a maximum output power not listed above, the recommended separation distance d in meters (m) can be estimated using the equation applicable to the frequency of the transmitter, where P is the maximum output power rating of the transmitter in watts (W) according to the transmitter manufacturer.
NOTE: At 80 MHz and 800 MHz, the separation distance for the higher frequency range applies.
NOTE: These guidelines may not apply in all situations. Electromagnetic propagation is affected by absorption and reflection from structures, objects, and people.

4. Disposal

- Contains Lithium-Ion Battery
  Lithium-Ion batteries may pose environmental and safety hazards and should be disposed of in accordance with all applicable Federal and State laws.
- Electronic Equipment
  Base should be properly disposed of in accordance with all applicable State and Federal laws.

5. Notes on Safety

Warnings and Recommendations

- Contains Lithium-Ion Battery
  Damage can cause fire. Do not puncture. Do not expose to excessive heat (≥ 50°C).
- Do not use after expiration date
  Expiration date is published on base label. Discontinue use if expiration date has passed.
- Inspect for device damage
  Do not use if package has been opened or damaged or if there is evidence of base damage. Doing so could result in injury.
- Tampering with parts in the Mydcombi™ Base
  Do not tamper with or attempt to open the base. Doing so could cause damage and result in personal injury.
- Risk of usage
  Failure to use base in accordance with instructions could affect dose dispensation. Keep base in upright position during use. If base has been idling for an extended period, dispense a waste spray. Optejet will not dispense drug while the base is actively charging.
- Risk due to insufficient user training
  Use base only with Mydcombi™ Cartridge. Refer to "Instructions for Use - Mydcombi™ Ophthalmic Spray".
- Risk due to battery leakage
  Do not use base if there is any sign of battery leakage.
- Keep dry
  Do not expose base to fluids; keep dry.
- Transportation and Storage
  Do not store or transport base with sharp or metallic objects.
- Risk of electrical leakage
  Non-hazardous voltage is present during normal use.
- Do not use with other equipment
- Do not use with non-certified USB charger
  Recharge base using a micro-USB cable (not included). Use of a charger other than that specified in Section 2 - Specifications could result in increased electromagnetic emissions or decreased electromagnetic immunity of the base, resulting in improper operation.
  CAUTION – For professional use
  Federal law restricts this device to sale by or on the order of a physician (21 CFR§801.109(b)(1)).
  CAUTION – Radiation emission
  This device emits electromagnetic radiation.

6. Reporting to Manufacturer and Authorities

If a serious incident occurs in connection with this device that affects the user or another person, please report incident to Eyenovia by calling 1-833-393-6684 (choose Option 1) or FDA at 1-800-FDA-1088 or http://www.fda.gov/medwatch.

7. Symbols Used in Labels on Mydcombi™ Base and Packaging

SYMBOL | DEFINITION |  | SYMBOL | DEFINITION
 | CAUTION, CONSULT ACCOMPANYING DOCUMENTS |  |  | USE BY (YYYY-MM: YEAR-MONTH)
 | SEE INSTRUCTIONS FOR USE |  |  | ELECTRONIC EQUIPMENT. DO NOT THROW IN TRASH.
 | CATALOG NUMBER |  |  | NON-STERILE
 | BATCH CODE |  |  | KEEP DRY
 | QUANTITY |  |  | LITHIUM-ION BATTERY - TO BE APPROPRIATELY RECYCLED
 | DATE OF MANUFACTURE (YYYY-MM : YEAR-MONTH) |  |  | MANUFACTURER
 | WARNING: ELECTRICITY |  |  | CAUTION: FEDERAL LAW RESTRICTS THIS PRODUCT
 | PROTECTED AGAINST VERTICALLY FALLING WATER DROPS UP TO 15-DEGREE ANGLE |  |  | TYPE BF PART COMPLYING WITH IEC 60601-1

MANUFACTURED BY | Contact / Return Goods Policy
Eyenovia, Inc. 8748 Technology Way, Reno, NV 89521 © 2022 Eyenovia, Inc. All rights reserved. www.eyenovia.com | Contact your sales representative or Eyenovia for product returns. Call 1-833-EYENOVIA (393-6684) admin@eyenovia.com

PRINCIPAL DISPLAY PANEL - MYDCOMBI Base Unit Label

MydCombi™ Base
Non-Sterile

REF FG-16427
LOT F-#####
YYYY-MM-DD

Li-ion

15°C
59°F

25°C
77°F

IPX2

Eyenovia, Inc.
295 Madison Ave, Ste 2400
New York, NY 10017

(01) 008600099909700
(10) F-123465
(17) 250405

Rx ONLY
LS-17076-E

PRINCIPAL DISPLAY PANEL - MYDCOMBI Base Unit Carton

eyenovia

Rx ONLY
LS-17075-D

REF FG-16427 MydCombi™ Base
LOT F-#####
QTY 1

USE BY YYYY-MM-DD

YYYY-MM-DD

Eyenovia, Inc.
295 Madison Ave, Ste 2400
New York, NY 10017

Li-ion

NON
STERILE

IPX2

15°C
59°F

25°C
77°F

PRINCIPAL DISPLAY PANEL - MYDCOMBI Base Single Carton Label

LS-17078-D

MydCombi™

Tropicamide and Phenylephrine
HCl Ophthalmic Spray 1% / 2.5 %

For Topical Ophthalmic Use

Exp: YYYY-MM
LOT ############

Manufactured for:
Eyenovia, Inc.
295 Madison Ave, Ste 2400
New York, NY 10017

NDC 81046-0111-1

Sterile 1.9mL Rx Only

PRINCIPAL DISPLAY PANEL - MYDCOMBI Base Single Carton

MydCombi™

Sterile

Rx Only

Tropicamide and Phenylephrine HCl
Ophthalmic Spray 1% / 2.5 %

MydCombi Cartridge
NDC 81046-0111-1

LOT ##########
QTY 1

YYYY-MM

Eyenovia, Inc.
295 Madison Ave, Ste 2400
New York, NY 10017

STORAGE
Store at room temperature 15°C to 25°C (59°F to 77°F).

PRINCIPAL DISPLAY PANEL - MYDCOMBI Cartridge and Base Carton

Rx ONLY
LS-17081-D

MydCombi™

NDC: 81046-0111-2

Tropicamide and Phenylephrine HCl Ophthalmic Spray 1% / 2.5 %

MydCombi Cartridge

STORAGE
Store at room temperature 15°C to 25°C (59°F to 77°F).
QTY 1

BASE UNIT

REF FG-16427 MydCombi Base
QTY 1

STORAGE
Store at room temperature 15°C to 25°C (59°F to 77°F).

Eyenovia, Inc.
295 Madison Avenue, Suite 2400
New York, NY 10017

Li-ion

NON
STERILE

IPX2

15°C
59°F

25°C
77°F

PRINCIPAL DISPLAY PANEL - MYDCOMBI Cartridge and Base 5 Pack Box

MydCombi™

QTY 5

Sterile
Rx Only

Tropicamide and
Phenylephrine HCl
Ophthalmic Spray 1% / 2.5 %

Eyenovia, Inc.
295 Madison Avenue, Suite 2400
New York, NY 10017

MydCombi Cartridge
NDC 81046-0111-5

STORAGE
Store at room temperature 15°C to 25°C (59°F to 77°F).

NDC: 81046-0111-05
SN: ABC098DEF765GHI432JK
EXP: YYYY-MM
Lot: MCL123

LOT ##########

YYYY-MM

LS-17079-E